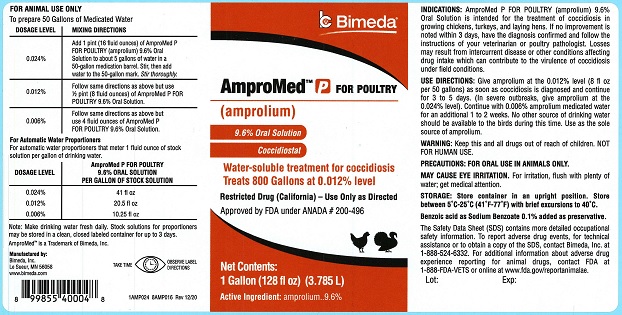 DRUG LABEL: AmproMed-P FOR POULTRY
NDC: 61133-8290 | Form: SOLUTION
Manufacturer: Bimeda Inc.
Category: animal | Type: OTC ANIMAL DRUG LABEL
Date: 20231212

ACTIVE INGREDIENTS: AMPROLIUM 96 mg/1 mL

INDICATIONS AND USAGE

AmproMed™ P FOR POULTRY

(amprolium)

9.6% Oral Solution Coccidiostat

Water-soluble treatment for coccidiosis

Treats 800 Gallons at 0.012% level.

Restricted Drug (California) – Use Only as Directed

Approved by FDA under ANADA # 200-496

Net Contents:

1 Gallon (128 fl oz) (3.785 L)

Active Ingredient: amprolium..............9.6%

INDICATIONS: AmproMed P FOR POULTRY (amprolium) 9.6 % Oral Solution is intended for the treatment of coccidiosis in growing chickens, turkeys, and laying hens. If no improvement is noted within 3 days, have the diagnosis confirmed and follow the instructions of your veterinarian or poultry pathologist. Losses may result from intercurrent disease or other conditions affecting drug intake which can contribute to the virulence of coccidiosis under field conditions.

DOSAGE AND ADMINISTRATION

USE DIRECTIONS: Give amprolium at the 0.012% level (8 fl oz per 50 gallons) as soon as coccidiosis is diagnosed and continue for three to five days. (In severe outbreaks, give amprolium at the 0.024% level). Continue with 0.006% amprolium medicated water for an additional 1 to 2 weeks. No other source of drinking water should be available to the birds during this time. Use as the sole source of amprolium.

FOR ANIMAL USE ONLY

To prepare 50 Gallons of Medicated Water

DOSAGE LEVEL | MIXING DIRECTIONS
0.024 % | Add 1 pint (16 fluid ounces) of AmproMed P FOR POULTRY (amprolium) 9.6% Oral Solution in about 5 gallons of water in a 50-gallon medication barrel. Stir, then add water to the 50-gallon mark. Stir thoroughly.
0.012 % | Follow same directions as above but use 1/2 pint (8 fluid ounces) of AmproMed P FOR POULTRY 9.6% Oral Solution.
0.006 % | Follow same directions as above but use 4 fluid ounces of AmproMed P FOR POULTRY 9.6% Oral Solution.

For Automatic Water Portioners

For automatic water proportioners that meter 1 fluid ounce of stock solution per gallon of drinking water.

DOSAGE LEVEL | AmproMed P FOR POULTRY 9.6 % ORAL SOLUTION; PER GALLON OF STOCK SOLUTION
0.024 % | 41 fl oz
0.012 % | 20.5 fl oz
0.006 % | 10.25 fl oz

Note:Make drinking water fresh daily. Stock solutions for proportioners may be stored in a clean, closed labeled container for up to 3 days.

WARNINGS

WARNING:Keep this and all drugs out of reach of children. NOT FOR HUMAN USE.

PRECAUTIONS: FOR ORAL USE IN ANIMALS ONLY.

MAY CAUSE EYE IRRITAION. For irritation, flush with plenty of water; get medical attention.

STORAGE AND HANDLING

STORAGE: Store container in an upright position. Store between 5°C - 25°C (41°F - 77°F) with brief excursions to 40°C.

Benzoic acid as Sodium Benzoate 0.1% added as preservative.

The Safety Data Sheet (SDS) contains more detailed occupational safety information. To report adverse drug events, for technical assistance or to obtain a copy of the SDS contact Bimeda, Inc. at 1-888-524-6332. For additional information about adverse drug experience reporting for animal drugs, contact FDA at 1-888-FDA-VETS or online at www.fda.gov/reportanimalae.

Manufactured by:

Bimeda, Inc.

Le Sueur, MN 56058